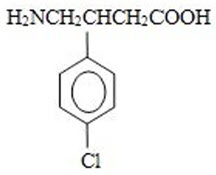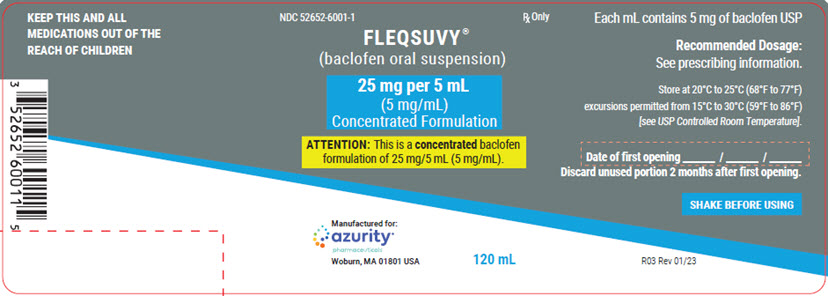 DRUG LABEL: FLEQSUVY
NDC: 52652-6001 | Form: SUSPENSION
Manufacturer: Azurity Pharmaceuticals, Inc.
Category: prescription | Type: HUMAN PRESCRIPTION DRUG LABEL
Date: 20251216

ACTIVE INGREDIENTS: BACLOFEN 5 mg/1 mL
INACTIVE INGREDIENTS: ANHYDROUS CITRIC ACID; D&C YELLOW NO. 10; FD&C RED NO. 40; HYDROXYETHYL CELLULOSE, UNSPECIFIED; PROPYLENE GLYCOL; WATER; DIMETHICONE; SILICON DIOXIDE; SODIUM BENZOATE; SUCRALOSE

HIGHLIGHTS OF PRESCRIBING INFORMATION

These highlights do not include all the information needed to use FLEQSUVY®safely and effectively. See full prescribing information for FLEQSUVY®.
FLEQSUVY®(baclofen oral suspension)
Initial U.S. Approval: 1977

RECENT MAJOR CHANGES

Dosage and Administations (2.3) 4/2024

1 INDICATIONS AND USAGE

- FLEQSUVY is a gamma-aminobutyric acid (GABA-ergic) agonist indicated for the treatment of spasticity resulting from multiple sclerosis, particularly for the relief of flexor spasms and concomitant pain, clonus, and muscular rigidity. (1)
- FLEQSUVY may also be of some value in patients with spinal cord injuries and other spinal cord diseases. (1)

Limitations of Use

FLEQSUVY is not indicated in the treatment of skeletal muscle spasm resulting from rheumatic disorders. (1)

2 DOSAGE AND ADMINISTRATION

- FLEQSUVY is a concentrated formulation. Verify the dose of the product prior to dispensing. (2.1)
- Initiate FLEQSUVY with a low dosage, preferably in divided doses, administered orally. Increase gradually based on clinical response and tolerability. (2.2)
- The maximum dosage is 80 mg daily (20 mg four times a day). (2.2)
- When discontinuing, reduce the dosage slowly. (2.3)

3 DOSAGE FORMS AND STRENGTHS

Oral Suspension: 25 mg per 5 mL (5 mg/mL) (3)

4 CONTRAINDICATIONS

- Hypersensitivity to baclofen (4)

5 WARNINGS AND PRECAUTIONS

- Abrupt discontinuation of baclofen has resulted in serious adverse reactions including death; therefore, reduce the dosage slowly when FLEQSUVY is discontinued. (5.1)
- Neonatal withdrawal symptoms can occur; gradually reduce the dosage and discontinue FLEQSUVY before delivery. (5.2)
- FLEQSUVY can cause drowsiness and sedation. Patients should avoid the operation of automobiles or other dangerous machinery until they know how the drug affects them. Advise patients that the central nervous system effects of FLEQSUVY may be additive to those of alcohol and other CNS depressants. (5.3)
- FLEQSUVY can cause exacerbation of the following: psychotic disorders, schizophrenia, or confusional states; autonomic dysreflexia; epilepsy. Use with caution in patients with these conditions. (5.5, 5.6, 5.7)

6 ADVERSE REACTIONS

- The most common (up to 15% or more) adverse reactions in patients were drowsiness, dizziness, and weakness. (6.1)

To report SUSPECTED ADVERSE REACTIONS, contact Azurity Pharmaceuticals at 1-800-461-7449 or FDA at 1-800-FDA-1088 or www.fda.gov/medwatch.

8 USE IN SPECIFIC POPULATIONS

- Pregnancy: Based on animal data, may cause fetal harm. (8.1)
- Because baclofen is excreted unchanged through the kidneys it may be necessary to reduce the dosage in patients with impaired renal function. (8.6)

FULL PRESCRIBING INFORMATION

1 INDICATIONS AND USAGE

FLEQSUVY is indicated for the treatment of spasticity resulting from multiple sclerosis, particularly for the relief of flexor spasms and concomitant pain, clonus, and muscular rigidity.

FLEQSUVY may also be of some value in patients with spinal cord injuries and other spinal cord diseases.

Limitations of Use

FLEQSUVY is not indicated in the treatment of skeletal muscle spasm resulting from rheumatic disorders.

2 DOSAGE AND ADMINISTRATION

2.1 Important Information

FLEQSUVY is a concentrated formulation. Verify the strength and the dose of the product prior to prescribing, dispensing, and administering.

2.2 Recommended Dosage

Initiate FLEQSUVY with a low dosage, preferably in divided doses, administered orally. The following gradually increasing dosage regimen is suggested, but should be adjusted based on clinical response and tolerability:

1 mL (5 mg) three times a day for three days
2 mL (10 mg) three times a day for three days
3 mL (15 mg) three times a day for three days
4 mL (20 mg) three times a day for three days

Additional increases may be necessary up to the maximum recommended dosage of 80 mg daily [4 mL (20 mg) four times a day].

2.3 Administration Instructions

Shake well FLEQSUVY oral suspension before administration. Discard unused portion 2 months after first opening.

A calibrated measuring device is recommended to measure and deliver the prescribed dose accurately. A household teaspoon or tablespoon is not an adequate measuring device.

Nasogastric Tube Administration

FLEQSUVY can be administered via a nasogastric (NG) tube at sizes 8 French or larger
using the following steps:

1. Ensure the NG feeding tube is flushed with appropriate amount of purified water (15 to 30 mL) prior to administration of FLEQSUVY.
2. Draw the required dose of FLEQSUVY in the appropriate oral or enteral syringe and administer the dose via the feeding tube. The medication may remain in the dosing syringe for up to 4 hours prior to administration.
3. If residual drug remains in the dosing syringe, draw up purified water into the syringe, shake gently, and administer through the feeding tube.
4. Flush the feeding tube with at least 25 mL of purified water.

2.4 Discontinuation of FLEQSUVY

When discontinuing FLEQSUVY, reduce the dosage slowly and avoid abrupt withdrawn from the drug to help minimize the risk of adverse reactions [see Warnings and Precautions (5.1)] .

3 DOSAGE FORMS AND STRENGTHS

Oral Suspension: 25 mg per 5 mL (5 mg/mL) baclofen as a concentrated orange to yellow- colored, grape-flavored suspension.

4 CONTRAINDICATIONS

FLEQSUVY is contraindicated in patients with hypersensitivity to baclofen.

5 WARNINGS AND PRECAUTIONS

5.1 Adverse Reactions from Abrupt Withdrawal of FLEQSUVY

Abrupt discontinuation of baclofen, regardless of the cause, has resulted in adverse reactions that include hallucinations, seizures, high fever, altered mental status, exaggerated rebound spasticity, and muscle rigidity, that in rare cases has advanced to rhabdomyolysis, multiple organ-system failure, and death. Therefore, reduce the dosage slowly when FLEQSUVY is discontinued, unless the clinical situation justifies a rapid withdrawal.

5.2 Neonatal Withdrawal Symptoms

Withdrawal symptoms in neonates whose mothers were treated with oral baclofen throughout pregnancy have been reported starting hours to days after delivery. The symptoms of withdrawal in these infants have included increased muscle tone, tremor, jitteriness, and seizure. If the potential benefit justifies the potential risk to the fetus and FLEQSUVY is continued during pregnancy, gradually reduce the dosage and discontinue FLEQSUVY before delivery. If slow withdrawal is not feasible, advise the parents or caregivers of the exposed neonate of the potential for neonatal withdrawal.

5.3 Drowsiness and Sedation

Drowsiness and sedation have been reported in up to 63% of patients taking baclofen, the active ingredient in FLEQSUVY [see Adverse Reactions (6.1)] . Patients should avoid operation of automobiles or other dangerous machinery and activities made hazardous by decreased alertness when starting FLEQSUVY or increasing the dose until they know how the drug affects them.

Advise patients that the central nervous system depressant effects of FLEQSUVY may be additive to those of alcohol and other CNS depressants.

5.4 Poor Tolerability in Stroke Patients

FLEQSUVY should be used with caution in patients who have had a stroke. Baclofen has not significantly benefited patients with stroke. These patients have also shown poor tolerability to the drug.

5.5 Exacerbation of Psychotic Disorders, Schizophrenia, or Confusional States

FLEQSUVY should be used with caution in patients suffering from psychotic disorders, schizophrenia, or confusional states. If treated with FLEQSUVY, these patients should be kept under careful surveillance because exacerbations of these conditions have been observed with oral baclofen administration.

5.6 Exacerbation of Autonomic Dysreflexia

FLEQSUVY should be used with caution in patients with a history of autonomic dysreflexia. The presence of nociceptive stimuli or abrupt withdrawal of FLEQSUVY may cause an autonomic dysreflexic episode.

5.7 Exacerbation of Epilepsy

FLEQSUVY should be used with caution in patients with epilepsy. Deterioration in seizure control has been reported in patients taking baclofen.

5.8 Posture and Balance Effects

FLEQSUVY should be used with caution in patients where spasticity is utilized to sustain upright posture and balance in locomotion or whenever spasticity is utilized to obtain increased function.

5.9 Ovarian Cysts

A dose-related increase in incidence of ovarian cysts was observed in female rats treated chronically with oral baclofen. Ovarian cysts have been found by palpation in about 4% of the multiple sclerosis patients who were treated with oral baclofen for up to one year. In most cases, these cysts disappeared spontaneously while patients continued to receive the drug. Ovarian cysts are estimated to occur spontaneously in approximately 1% to 5% of the normal female population.

6 ADVERSE REACTIONS

The following clinically significant adverse reactions are described elsewhere in the labeling:

- Adverse Reactions from Abrupt Withdrawal of FLEQSUVY [see Warnings and Precautions (5.1)]
- Neonatal Withdrawal Symptoms [see Warnings and Precautions (5.2)]
- Drowsiness and Sedation [see Warnings and Precautions (5.3)]
- Poor Tolerability in Stroke Patients [see Warnings and Precautions (5.4)]
- Exacerbation of Psychotic Disorders, Schizophrenia, or Confusional States [see Warnings and Precautions (5.5)]
- Exacerbation of Autonomic Dysreflexia [see Warnings and Precautions (5.6)]
- Exacerbation of Epilepsy [see Warnings and Precautions (5.7)]
- Posture and Balance Effects [see Warnings and Precautions (5.8)]
- Ovarian Cysts [see Warnings and Precautions (5.9)]

6.1 Clinical Trials Experience

Because clinical trials are conducted under widely varying conditions, adverse reaction rates observed in the clinical trials of a drug cannot be directly compared to rates in the clinical trials of another drug and may not reflect the rates observed in practice.

The most common adverse reaction is transient drowsiness. In one controlled study of 175 patients, transient drowsiness was observed in 63% of those receiving baclofen compared to 36% of those in the placebo group. Other common adverse reactions (up to 15%) are dizziness and weakness. Adverse reactions with a frequency of ≥1% are listed in Table 1.

Table 1. Common (≥1%) Adverse Reactions in Patients Treated with Baclofen for Spasticity
ADVERSE REACTION | PERCENT
Drowsiness | 10-63%
Dizziness | 5-15%
Weakness | 5-15%
Nausea | 4-12%
Confusion | 1-11%
Hypotension | 0-9%
Headache | 4-8%
Insomnia | 2-7%
Constipation | 2-6%
Urinary Frequency | 2-6%
Fatigue | 2-4%

The following adverse reactions not included in Table 1, classified by body system, were also reported:

Neuropsychiatric:euphoria, excitement, depression, hallucinations, paresthesia, muscle pain, tinnitus, slurred speech, coordination disorder, tremor, rigidity, dystonia, ataxia, blurred vision, nystagmus, strabismus, miosis, mydriasis, diplopia, dysarthria, epileptic seizure

Cardiovascular:dyspnea, palpitation, chest pain, syncope

Gastrointestinal:dry mouth, anorexia, taste disorder, abdominal pain, vomiting, diarrhea, and positive test for occult blood in stool

Genitourinary:enuresis, urinary retention, dysuria, impotence, inability to ejaculate, nocturia, hematuria

Other:rash, pruritus, ankle edema, excessive perspiration, weight gain, nasal congestion

The following laboratory tests have been found to be abnormal in patients receiving baclofen: increased SGOT, elevated alkaline phosphatase, and elevation of blood sugar.

7 DRUG INTERACTIONS

7.1 CNS Depressants and Alcohol

FLEQSUVY can cause CNS depression, including drowsiness and sedation, which may be additive when used concomitantly with other CNS depressants or alcohol [see Warnings and Precautions (5.3)] .

8 USE IN SPECIFIC POPULATIONS

8.1 Pregnancy

Risk Summary

There are no adequate data on the risk of major birth defects, miscarriages, or other maternal adverse outcomes associated with the use of FLEQSUVY in pregnant women. There are adverse effects on fetal outcomes associated with withdrawal from baclofen after delivery (see Clinical Considerations) . Oral administration of baclofen to pregnant rats resulted in an increased incidence of fetal structural abnormalities at a dose that was also associated with maternal toxicity. The background risk of major birth defects and miscarriage for the indicated population is unknown. In the U.S. general population, the estimated background risk of major birth defects and miscarriage in clinically recognized pregnancies is 2-4% and 15-20%, respectively.

Clinical Considerations

Fetal/Neonatal Adverse Reactions

FLEQSUVY may increase the risk of late-onset neonatal withdrawal symptoms [see Warnings and Precautions (5.2)] .

Data

Animal Data

Baclofen given orally has been shown to increase the incidence of omphaloceles (ventral hernias) in fetuses of rats given approximately 13 times on a mg/kg basis, or 3 times on a mg/m^2basis, the maximum oral dose recommended for human use; this dose also caused reductions in food intake and weight gain in the dams. This abnormality was not seen in mice or rabbits.

8.2 Lactation

Risk Summary

At recommended oral doses, baclofen is present in human milk. There are no human data on the effects of baclofen on milk production. Withdrawal symptoms can occur in breastfed infants when maternal administration of FLEQSUVY is stopped, or when breastfeeding is stopped [see Warnings and Precautions (5.2)] . There are no adequate data on other effects of baclofen on the breastfed infant.

The developmental and health benefits of breastfeeding should be considered along with the mother’s clinical need for FLEQSUVY and any potential adverse effects on the breastfed infant from FLEQSUVY or from the underlying maternal condition.

8.4 Pediatric Use

Safety and effectiveness in pediatric patients below the age of 12 have not been established.

8.5 Geriatric Use

In general, dose selection for an elderly patient should be cautious, usually starting at the low end of the dosing range, reflecting the greater frequency of decreased hepatic, renal, or cardiac function, and of concomitant disease or other drug therapy. This drug is known to be substantially excreted by the kidney, and the risk of adverse reactions to this drug may be greater in patients with impaired renal function. Because elderly patients are more likely to have decreased renal function, care should be taken in dose selection, and it may be useful to monitor renal function [see Use in Specific Populations (8.6)] .

8.6 Renal Impairment

Because baclofen is primarily excreted unchanged through the kidneys, FLEQSUVY should be given with caution to patients with renal impairment, and it may be necessary to reduce the dosage.

10 OVERDOSAGE

10.1 Symptoms of Baclofen Overdose

With overdose of baclofen, patients may present in coma or with progressive drowsiness, lightheadedness, dizziness, somnolence, accommodation disorders, respiratory depression, seizures, or hypotonia progressing to loss of consciousness.

10.2 Treatment for Overdose

The treatment of baclofen overdose includes gastric decontamination, maintaining an adequate airway and respirations.

11 DESCRIPTION

FLEQSUVY (baclofen oral suspension) is a gamma-aminobutyric acid (GABA-ergic) agonist available as 25 mg per 5 mL (5 mg/mL) suspension for oral administration. Its chemical name is 4-amino-3-(4-chlorophenyl)-butanoic acid, and its structural formula is:

Molecular formula is C10H12C1NO2.
Molecular Weight is 213.66 g/mol.

Baclofen USP is a white to off-white, odorless or practically odorless crystalline powder. It is slightly soluble in water, very slightly soluble in methanol, and insoluble in chloroform.

The FLEQSUVY (baclofen oral suspension) inactive ingredients are: artificial grape flavor, citric acid anhydrous, D&C yellow No. 10, FD&C red No. 40, hydroxyethyl cellulose, propylene glycol, purified water, simethicone emulsion, sodium benzoate, and sucralose.

12 CLINICAL PHARMACOLOGY

12.1 Mechanism of Action

The precise mechanism of action of baclofen is not fully understood. Baclofen inhibits both monosynaptic and polysynaptic reflexes at the spinal level, possibly by decreasing excitatory neurotransmitter release from afferent terminals, although actions at supraspinal sites may also occur and contribute to its clinical effect. Baclofen is a structural analog of the inhibitory neurotransmitter gamma- aminobutyric acid (GABA) and may exert its effects by stimulation of the GABABreceptor subtype.

12.2 Pharmacodynamics

Baclofen has been shown to have general CNS depressant properties, as indicated by the production of sedation with tolerance, somnolence, ataxia, and respiratory and cardiovascular depression [see Warnings and Precautions (5.3), Adverse Reactions (6.1), and Overdosage (10.1)] .

12.3 Pharmacokinetics

A pharmacokinetic study in heathy adult male and female subjects under fasting conditions at 20 mg dose level demonstrated similar bioavailability for baclofen oral suspension and oral tablets.

Absorption

The peak plasma concentrations of baclofen were achieved in about 1 hour from administration of FLEQSUVY oral suspension in the fasted state, and the apparent elimination half-life is about 5.6 hours.

Effect of Food

Administration of FLEQSUVY with a high-fat meal resulted in 9% decrease in AUC and 33% decrease in Cmaxcompared to the fasted state.

Elimination

Baclofen is excreted primarily by the kidney in unchanged form, and there is relatively large intersubject variation in absorption and/or elimination.

13 NONCLINICAL TOXICOLOGY

13.1 Carcinogenesis, Mutagenesis, Impairment of Fertility

Carcinogenesis

No increase in tumors was seen in rats receiving baclofen orally for two years at approximately 30 to 60 times on a mg/kg basis, or 10 to 20 times on a mg/m^2basis, the maximum oral dose recommended for human use.

Mutagenesis

Genetic toxicology assays have not been conducted for baclofen.

Impairment of Fertility

Studies to evaluate the effects of baclofen on fertility have not been conducted.

14 CLINICAL STUDIES

The efficacy of FLEQSUVY is based upon a bioavailability study in healthy adults comparing baclofen oral tablets to FLEQSUVY [see Clinical Pharmacology (12.3)] .

16 HOW SUPPLIED/STORAGE AND HANDLING

16.1 How Supplied

FLEQSUVY (baclofen oral suspension) contains 25 mg per 5 mL (5 mg/mL) baclofen. It is a concentrated orange to yellow-colored, grape-flavored suspension and is supplied in high-density polyethylene (HDPE) bottles with white, polypropylene, child-resistant closures with a foam liner and heat induction layered inner seal.

120 mL, NDC 52652-6001-1

300 mL, NDC 52652-6001-2

16.2 Storage and Handling

Store at 20°C to 25°C (68°F to 77°F); excursions permitted between 15° and 30° (59° and 86° F) (see USP Controlled Room Temperature).

Discard unused portion 2 months after first opening.

17 PATIENT COUNSELING INFORMATION

Administration Instructions

Inform patients that FLEQSUVY is a concentrated formulation. Instruct patients or caregivers to use an oral dosing syringe and not to use a household teaspoon to correctly measure the prescribed amount of medication. Inform patients that oral dosing syringes may be obtained from their pharmacy. Instruct patients to shake before using [see Dosage and Administration (2.1, 2.3)] .

Risks Related to Sudden Withdrawal of FLEQSUVY

Advise patients and caregivers not to discontinue use of FLEQSUVY without consulting with their healthcare provider because sudden withdrawal of FLEQSUVY can result in serious complications that include hallucinations, seizures, high fever, confusion, muscle stiffness, multiple organ-system failure, and death [see Warnings and Precautions (5.1)] . Inform patients that early symptoms of FLEQSUVY withdrawal may include increased spasticity, itching, and tingling of extremities.

Neonatal Withdrawal Symptoms

Advise patients to notify their healthcare provider if they are pregnant, plan to become pregnant, or plan to breastfeed [see Warnings and Precautions (5.2) and Use in Specific Populations (8.2)] .

Increased Risk of Drowsiness with Alcohol and Other CNS Depressants

Advise patients that FLEQSUVY may cause drowsiness, and that they should avoid the operation of automobiles or other dangerous machinery, or activities made hazardous by decreased alertness when starting FLEQSUVY or increasing the dose until they know how the drug affects them [see Warnings and Precautions (5.3)] . Inform patients and their caregivers that the drowsiness associated with FLEQSUVY use can be worsened by alcohol and other CNS depressants. Advise patients to read all medicine labels carefully, and to tell their healthcare provider about all prescription and nonprescription drugs they may use.

Storage

Instruct patients to store FLEQSUVY at room temperature and to discard unused portion 2 months after first opening [see How Supplied/Storage and Handling (16.2)] .

FLEQSUVY is a registered trademark of Azurity Pharmaceuticals, Inc.

Manufactured for:

Azurity Pharmaceuticals, Inc.
Woburn, MA 01801

Patent: https://azurity.com/patents

This product’s labeling may have been updated. For current Full Prescribing Information, please visit www.FLEQSUVY.com

PN: 65628-00623

REV: 02 04/2024

PRINCIPAL DISPLAY PANEL - Bottle Label

NDC 52652-6001-1 Rx Only

FLEQSUVY®
(baclofen oral suspension)

25 mg per 5 mL
(5 mg/mL)
Concentrated Formulation

ATTENTION:This is a concentratedbaclofen
formulation of 25 mg/5 mL (5 mg/mL).

Manufactured for:
azurity®
pharmaceuticals
Woburn, MA 01801 USA

120 mL

KEEP THIS AND ALL
MEDICATIONS OUT OF THE
REACH OF CHILDREN

Each mL contains 5 mg of baclofen USP

Recommended Dosage:
See prescribing information.

Store at 20°C to 25°C (68°F to 77°F)
excursions permitted from 15°C to 30°C (59°F to 86°F)
[see USP Controlled Room Temperature].

Date of first opening _______ / _______ / _______
Discard unused portion 2 months after first opening.

SHAKE BEFORE USING